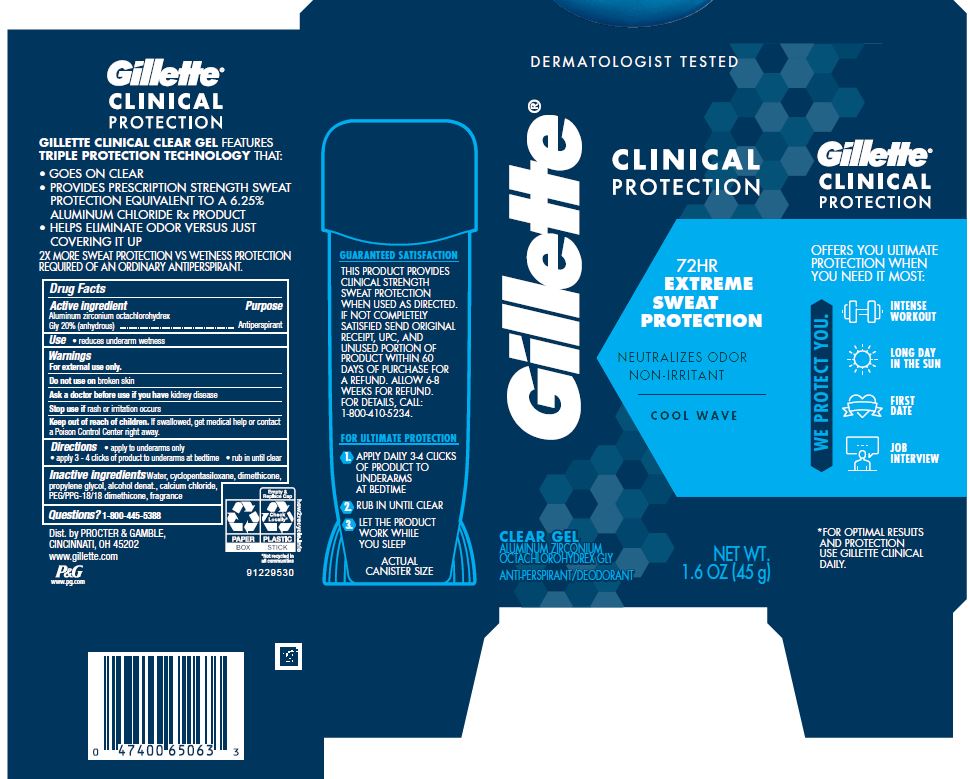 DRUG LABEL: Gillette Clinical Protection Cool Wave Clear
NDC: 69423-584 | Form: GEL
Manufacturer: The Procter & Gamble Manufacturing Company
Category: otc | Type: HUMAN OTC DRUG LABEL
Date: 20250306

ACTIVE INGREDIENTS: ALUMINUM ZIRCONIUM OCTACHLOROHYDREX GLY 20 g/100 g
INACTIVE INGREDIENTS: TETRAHYDROLINALYL ACETATE; ORANGE TERPENES; CYCLOMETHICONE 5; WATER; DIMETHICONE; PROPYLENE GLYCOL; CALCIUM CHLORIDE; PEG/PPG-18/18 DIMETHICONE; ALCOHOL; TETRAHYDROLINALOOL; LINALOOL, (+/-)-; BENZYL SALICYLATE; .BETA.-CITRONELLOL, (R)-; COUMARIN; LIMONENE, (+)-; DIHYDROMYRCENOL; LINALYL ACETATE; CITRAL; CITRONELLYL NITRILE, (+/-)-; DIPROPYLENE GLYCOL; HEXAMETHYLINDANOPYRAN; ALLYL AMYL GLYCOLATE

Gillette® Clinical Protection Cool Wave Clear Gel

Drug Facts

Active ingredient

Aluminum zirconium octachlorohydrex Gly 20% (anhydrous)

Purpose

Antiperspirant

Use

reduces underarm wetness

Warnings

For external use only.

Do not use on broken skin

Ask a doctor before use if you have kidney disease

Stop use if rash or irritation occurs

Keep out of reach of children. If swallowed, get medical help or contact a Poison Control Center right away.

Directions

- apply to underarms only
- apply 3 - 4 clicks of product to underarms at bedtime
- rub in until clear

Inactive ingredients

water, cyclopentasiloxane, dimethicone, propylene glycol, alcohol denat., calcium chloride, PEG/PPG-18/18 dimethicone, fragrance

Questions?

1-800-445-5388

Dist. by PROCTER & GAMBLE,
CINCINNATI, OH 45202.

PRINCIPAL DISPLAY PANEL - 45 g Canister Carton

Gillette®

CLINICAL

PROTECTION

72 HR

EXTREME

SWEAT PROTECTION

COOL WAVE
CLEAR GEL

ALUMINUM ZIRCONIUM

OCTACHLOROHYDREX GLY
ANTI-PERSPIRANT/DEODORANT

NET WT. 1.6 OZ. (45 g)